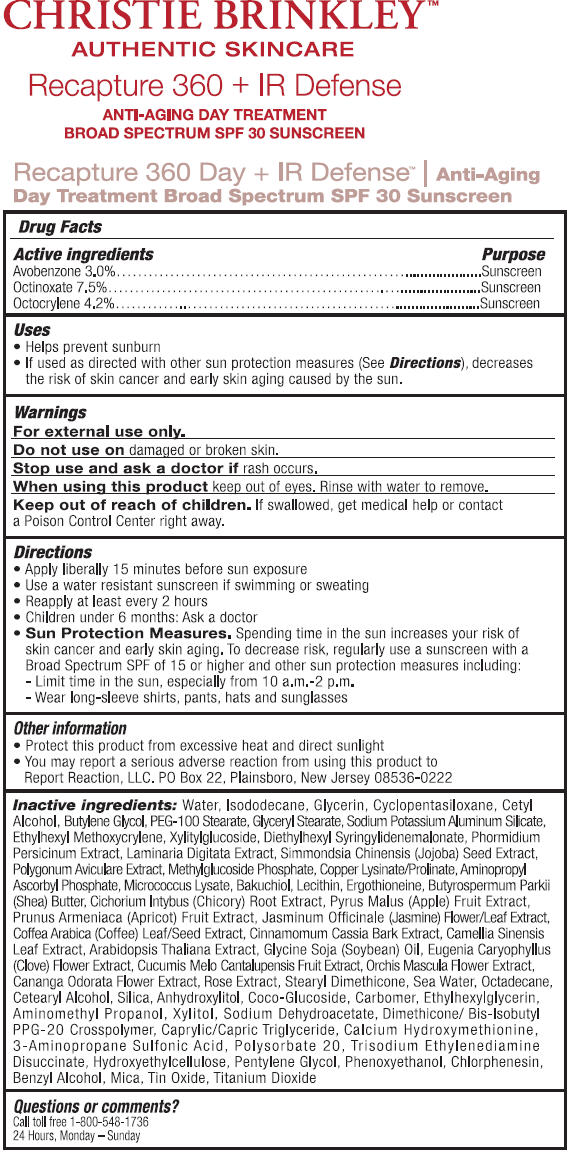 DRUG LABEL: Recapture 360 Day plus IR Defense
NDC: 70550-001 | Form: CREAM
Manufacturer: Atlantic Coast Media Group, LLC.
Category: otc | Type: HUMAN OTC DRUG LABEL
Date: 20170124

ACTIVE INGREDIENTS: AVOBENZONE 30 mg/1 mL; OCTOCRYLENE 42 mg/1 mL; OCTINOXATE 75 mg/1 mL
INACTIVE INGREDIENTS: ISODODECANE; CYCLOMETHICONE 5; CETYL ALCOHOL; BUTYLENE GLYCOL; GLYCERIN; GLYCERYL MONOSTEARATE; PEG-100 STEARATE; ETHYLHEXYL METHOXYCRYLENE; XYLITYLGLUCOSIDE; DIETHYLHEXYL SYRINGYLIDENEMALONATE; PHORMIDIUM PERSICINUM; LAMINARIA DIGITATA; SIMMONDSIA CHINENSIS SEED; POLYGONUM AVICULARE TOP; AMINOPROPYL ASCORBYL PHOSPHATE; BAKUCHIOL; ERGOTHIONEINE; .ALPHA.-TOCOPHEROL ACETATE; SHEA BUTTER; CHICORY ROOT; APPLE; APRICOT; JASMINUM OFFICINALE FLOWER; ARABICA COFFEE BEAN; CHINESE CINNAMON; GREEN TEA LEAF; ARABIDOPSIS THALIANA; SOYBEAN OIL; CLOVE; CANTALOUPE; ORCHIS MASCULA FLOWER; CANANGA ODORATA FLOWER; STEARYL DIMETHICONE (400 MPA.S AT 50C); SODIUM CHLORIDE; OCTADECANE; CETOSTEARYL ALCOHOL; SILICON DIOXIDE; ANHYDROXYLITOL; COCO GLUCOSIDE; CARBOXYPOLYMETHYLENE; ETHYLHEXYLGLYCERIN; AMINOMETHYLPROPANOL; XYLITOL; SODIUM DEHYDROACETATE; MEDIUM-CHAIN TRIGLYCERIDES; DIMETHICONE/BIS-ISOBUTYL PPG-20 CROSSPOLYMER; DESMENINOL CALCIUM; TRAMIPROSATE; POLYSORBATE 20; EDETATE DISODIUM; HYDROXYETHYL CELLULOSE (100 MPA.S AT 2%); PENTYLENE GLYCOL; PHENOXYETHANOL; CHLORPHENESIN; BENZYL ALCOHOL; MICA; STANNIC OXIDE; TITANIUM DIOXIDE

Recapture 360 Day + IR Defense

Drug Facts

ACTIVE INGREDIENT

Active ingredients | Purpose
Avobenzone 3.0% | Sunscreen
Octinoxate 7.5% | Sunscreen
Octocrylene 4.2% | Sunscreen

Uses

- Helps prevent sunburn
- If used as directed with other sun protection measures (See Directions), decreases the risk of skin cancer and early skin aging caused by the sun.

Warnings

For external use only.

Do not use on damaged or broken skin.

Stop use and ask a doctor if rash occurs.

When using this product keep out of eyes. Rinse with water to remove.

Keep out of reach of children. If swallowed, get medical help or contact a Poison Control Center right away.

Directions

- Apply liberally 15 minutes before sun exposure
- Use a water resistant sunscreen if swimming or sweating
- Reapply at least every 2 hours
- Children under 6 months: Ask a doctor
- Sun Protection Measures. Spending time in the sun increases your risk of skin cancer and early skin aging. To decrease risk, regularly use a sunscreen with a Broad Spectrum SPF of 15 or higher and other sun protection measures including:
  - Limit time in the sun, especially from 10 a.m. –2 p.m.
  - Wear long-sleeve shirts, pants, hats and sunglasses

Other information

- Protect the product in this container from excessive heat and direct sunlight
- You may report a serious adverse reaction from using this product to Report Reaction, LLC.

PO Box 22, Plainsboro, NJ 08536-0222

Inactive ingredients

Water, Isododecane, Cyclopentasiloxane, Cetyl Alcohol, Butylene Glycol, Glycerin, Glyceryl Stearate, PEG-100 Stearate, Sodium Potassium Aluminum Silicate, Ethylhexyl Methoxycrylene, Xylitylglucoside, Diethylhexyl Syringylidenemalonate, Phormidium Persicinum Extract, Laminaria Digitata Extract, Simmondsia Chinensis (Jojoba) Seed Extract, Polygonum Aviculare Extract, Methylglucoside Phosphate, Copper Lysinate/Prolinate, Aminopropyl Ascorbyl Phosphate, Micrococcus Lysate, Bakuchiol, Lecithin, Ergothioneine, Tocopheryl Acetate, Butyrospermum Parkii (Shea) Butter, Cichorium Intybus (Chicory) Root Extract, Pyrus Malus (Apple) Fruit Extract, Prunus Armeniaca (Apricot) Fruit Extract, Jasminum Officinale (Jasmine) Flower/Leaf Extract, Coffea Arabica (Coffee) Leaf/Seed Extract, Cinnamomum Cassia Bark Extract, Camellia Sinensis Leaf Extract, Arabidopsis Thaliana Extract, Glycine Soja (Soybean) Oil, Eugenia Caryophyllus (Clove) Flower Extract, Cucumis Melo Cantalupensis Fruit Extract, Orchis Mascula Flower Extract, Cananga Odorata Flower Extract, Rose Extract, Stearyl Dimethicone, Sea Water, Octadecane, Cetearyl Alcohol, Silica, Anhydroxylitol, Coco-Glucoside, Carbomer, Ethylhexylglycerin, Aminomethyl Propanol, Xylitol, Sodium Dehydroacetate, Dimethicone/Bis-Isobutyl PPG-20 Crosspolymer, Caprylic/Capric Triglyceride, Calcium Hydroxymethionine, 3-Aminopropane Sulfonic Acid, Polysorbate 20, Disodium EDTA, Hydroxyethylcellulose, Pentylene Glycol, Phenoxyethanol, Chlorphenesin, Benzyl Alcohol, Mica, Tin Oxide, Titanium Dioxide

Questions or Comments?

Call Toll-Free 1-800-548-1736
24 Hours, Monday – Sunday

PRINCIPAL DISPLAY PANEL - Jar Label

CHRISTIE BRINKLEY™
AUTHENTIC SKINCARE

Recapture 360 + IR Defense

ANTI-AGING DAY TREATMENT
BROAD SPECTRUM SPF 30 SUNSCREEN